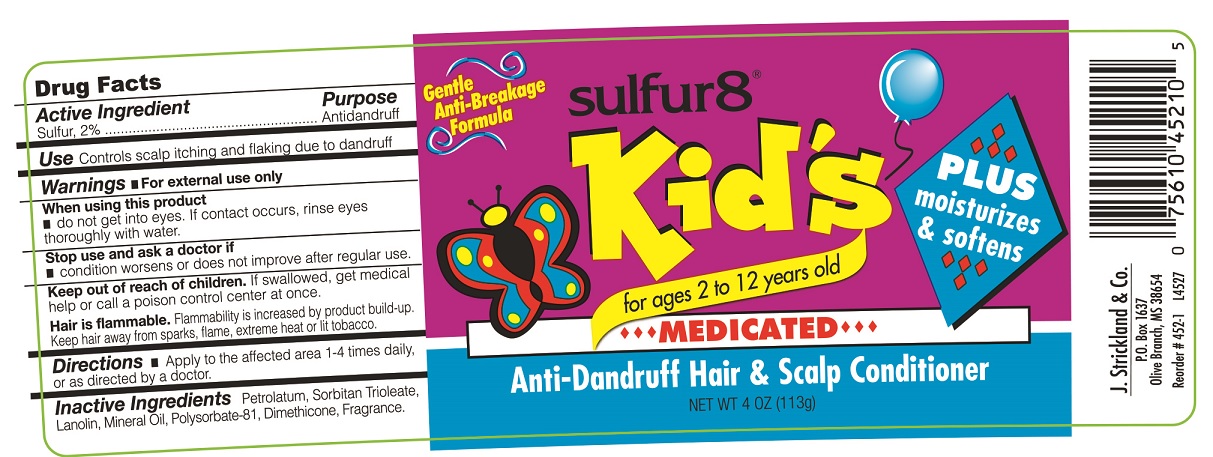 DRUG LABEL: Sulfur 8 Kids Anti-Dandruff Hair and Scalp Conditioner
NDC: 12022-022 | Form: OINTMENT
Manufacturer: J. Strickland & Co.
Category: otc | Type: HUMAN OTC DRUG LABEL
Date: 20251103

ACTIVE INGREDIENTS: SULFUR 20 mg/1 g
INACTIVE INGREDIENTS: PETROLATUM; SORBITAN TRIOLEATE; LANOLIN; MINERAL OIL; POLYSORBATE 81; DIMETHICONE

Sulfur 8 Kids Anti-Dandruff Hair and Scalp Conditioner

Active Ingredients

Sulfur, 2%

Purpose

Antidandruff

Use:

controls scalp itching and flaking due to dandruff

Warnings:

For external use only

When using this product

- do not get into eyes. If contact occurs, rinse eyes thoroughly with water.

Stop use and consult a doctor if

- conditions worsens or does not improve after regular use.

Keep out of reach of children

If swallowed, get medical help or call a Poison Control Center right away.

Directions

- shake well
- for best results, use twice a week
- wet hair, apply shampoo, lather, rinse & repeat

Inactive Ingredients

SD Alcohol 40, Water, Propylene Glycol, Benzyl Alcohol, Menthol.